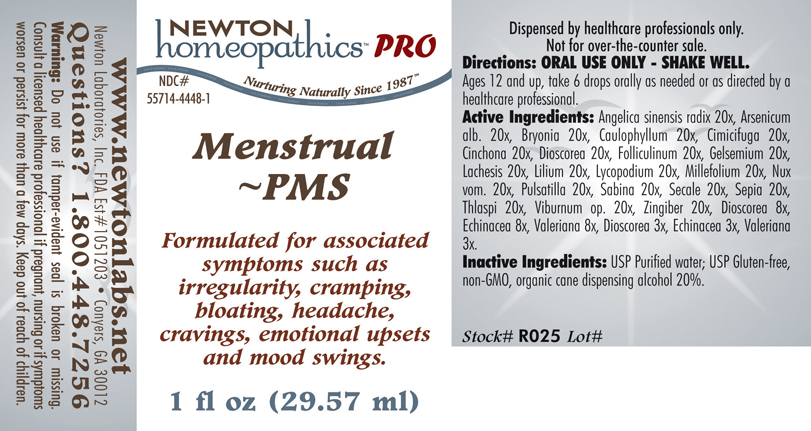 DRUG LABEL: Menstrual - PMS 
NDC: 55714-4448 | Form: LIQUID
Manufacturer: Newton Laboratories, Inc.
Category: homeopathic | Type: HUMAN PRESCRIPTION DRUG LABEL
Date: 20110601

ACTIVE INGREDIENTS: Angelica Sinensis Root 20 [hp_X]/1 mL; Arsenic Trioxide 20 [hp_X]/1 mL; Bryonia Alba Root 20 [hp_X]/1 mL; Caulophyllum Thalictroides Root 20 [hp_X]/1 mL; Black Cohosh 20 [hp_X]/1 mL; Cinchona Officinalis Bark 20 [hp_X]/1 mL; Dioscorea Villosa Tuber 20 [hp_X]/1 mL; Estrone 20 [hp_X]/1 mL; Gelsemium Sempervirens Root 20 [hp_X]/1 mL; Lachesis Muta Venom 20 [hp_X]/1 mL; Lilium Lancifolium Whole Flowering 20 [hp_X]/1 mL; Lycopodium Clavatum Spore 20 [hp_X]/1 mL; Achillea Millefolium 20 [hp_X]/1 mL; Strychnos Nux-vomica Seed 20 [hp_X]/1 mL; Pulsatilla Vulgaris 20 [hp_X]/1 mL; Juniperus Sabina Leafy Twig 20 [hp_X]/1 mL; Claviceps Purpurea Sclerotium 20 [hp_X]/1 mL; Sepia Officinalis Juice 20 [hp_X]/1 mL; Capsella Bursa-pastoris 20 [hp_X]/1 mL; Viburnum Opulus Bark 20 [hp_X]/1 mL; Ginger 20 [hp_X]/1 mL; Echinacea, Unspecified 8 [hp_X]/1 mL; Valerian 8 [hp_X]/1 mL
INACTIVE INGREDIENTS: Alcohol

Menstrual - PMS

INDICATIONS & USAGE SECTION

Menstrual - PMS Formulated for associated symptoms such as irregularity, cramping, bloating, headache, cravings, emotional upsets and mood swings.

DOSAGE & ADMINISTRATION SECTION

Directions: ORAL USE ONLY - SHAKE WELL. Ages 12 and up, take 6 drops orally as needed or as directed by a healthcare professional.

ACTIVE INGREDIENT SECTION

Angelica sinensis radix 20x, Arsenicum alb. 20x, Bryonia 20x, Caulophyllum 20x, Cimicifuga 20x, Cinchona 20x, Dioscorea 20x, Folliculinum 20x, Gelsemium 20x, Lachesis 20x, Lilium 20x, Lycopodium 20x, Millefolium 20x, Nux vom. 20x, Pulsatilla 20x, Sabina 20x, Secale 20x, Sepia 20x, Thlaspi 20x, Viburnum op. 20x, Zingiber 20x, Dioscorea 8x, Echinacea 8x, Valeriana 8x, Dioscorea 3x, Echinacea 3x, Valeriana 3x.

PURPOSE SECTION

Formulated for associated symptoms such as irregularity, cramping, bloating, headache, cravings, emotional upsets and mood swings.

INACTIVE INGREDIENT SECTION

Inactive Ingredients: USP Purified Water; USP Gluten-free, non-GMO, organic cane dispensing alcohol 20%.

QUESTIONS? SECTION

www.newtonlabs.net Newton Laboratories, Inc. FDA Est # 1051203 - Conyers, GA 30012
Questions? 1.800.448.7256

WARNINGS SECTION

Warning: Do not use if tamper - evident seal is broken or missing. Consult a licensed healthcare professional if pregnant, nursing or if symptoms worsen or persist for more than a few days. Keep out of reach of children.

PREGNANCY OR BREAST FEEDING SECTION

Consult a licensed healthcare professional if pregnant, nursing or if symptoms worsen or persist for more than a few days.

KEEP OUT OF REACH OF CHILDREN SECTION

Keep out of reach of children.